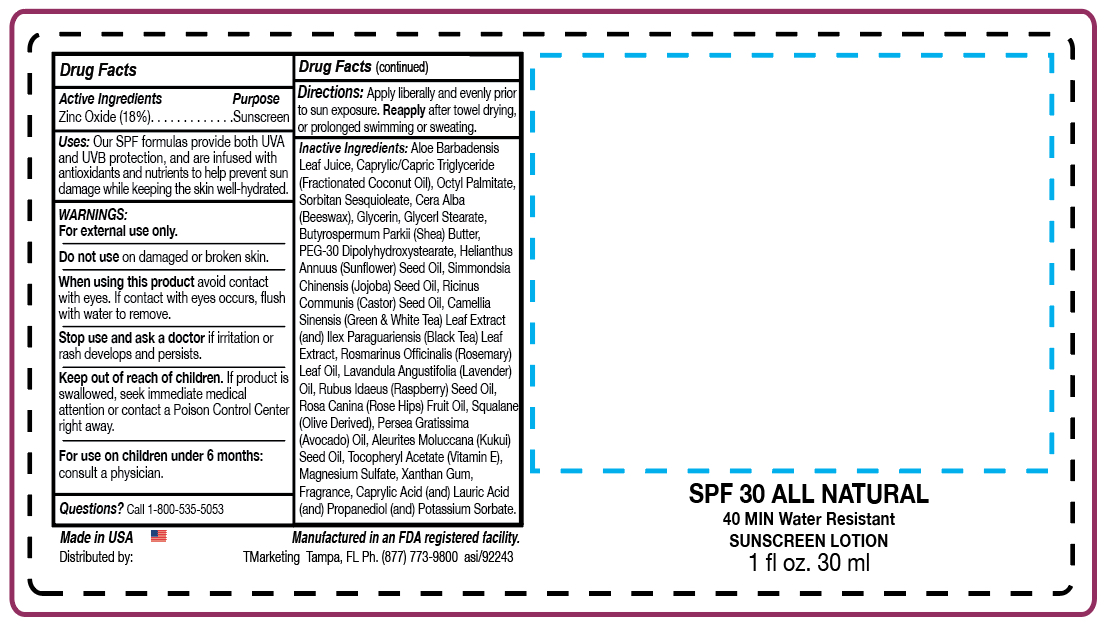 DRUG LABEL: Fresh Skin Organics
NDC: 58418-425 | Form: LOTION
Manufacturer: Tropical Enterprises International, Inc.
Category: otc | Type: HUMAN OTC DRUG LABEL
Date: 20200308

ACTIVE INGREDIENTS: ZINC OXIDE 6.05 g/30 mL
INACTIVE INGREDIENTS: POTASSIUM SORBATE; PROPANEDIOL; CASTOR OIL; ROSEMARY OIL; LAVENDER OIL; KUKUI NUT OIL; ALOE VERA LEAF; GLYCERYL MONOSTEARATE; ETHYLHEXYL PALMITATE; SORBITAN SESQUIOLEATE; GLYCERIN; SHEA BUTTER; JOJOBA OIL; YELLOW WAX; LAURIC ACID; CAPRYLIC/CAPRIC/LAURIC TRIGLYCERIDE; AVOCADO OIL; XANTHAN GUM; PEG-30 DIPOLYHYDROXYSTEARATE; ROSA CANINA FRUIT OIL; .ALPHA.-TOCOPHEROL ACETATE, D-; MAGNESIUM SULFATE, UNSPECIFIED; CAPRYLIC ACID; SUNFLOWER OIL; CAMELLIA SINENSIS WHOLE; ILEX PARAGUARIENSIS LEAF; RASPBERRY SEED OIL; SQUALANE

Formula: ABNZ2000

Active Ingredients:

Zinc Oxide (18%)

Purpose: Sunscreen

INDICATIONS AND USAGE

Uses: Our SPF formulas provide both UVA and UVB

protection, and are infused with antioxidants and nutrients to help

prevent sun damage while keepingthe skin well-hydrated.

WARNINGS:

For external use only.

Do not use on damaged or broken skin.

When using this product avoid contact with eyes.

If contact with eyes occurs, flush with water to remove.

Stop use and ask a doctor if irritation or rash develops

and persists.

Keep out of reach of children. If product is swallowed,

seek immediate medical attention or contact a Poison Control Center

right away.

For use on children under 6 months: consult a physician.

Questions? Call 1-800-535-5053